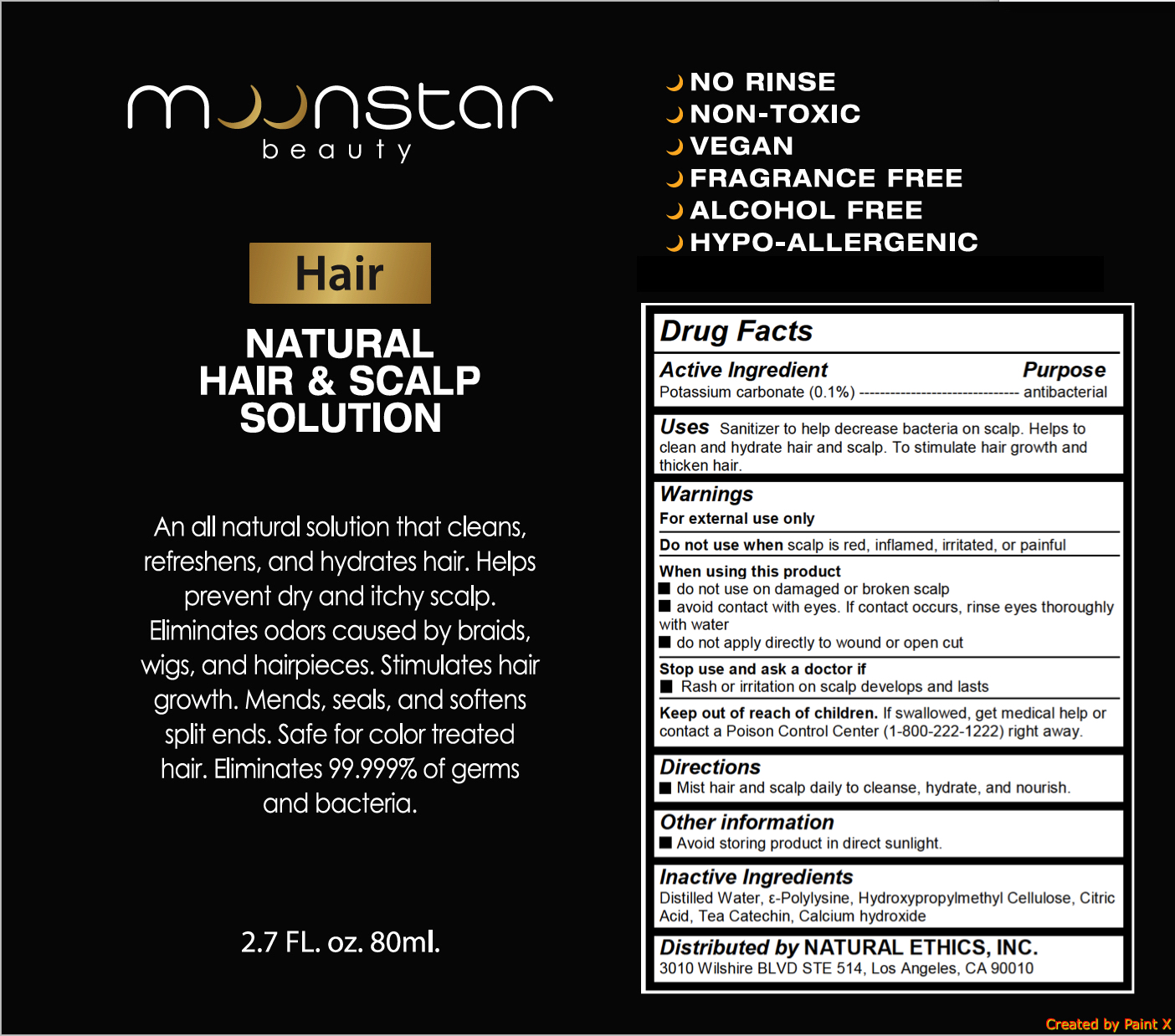 DRUG LABEL: MOONSTAR HAIR MIST
NDC: 72111-101 | Form: SPRAY
Manufacturer: NATURAL ETHICS, INC.
Category: otc | Type: HUMAN OTC DRUG LABEL
Date: 20180301

ACTIVE INGREDIENTS: POTASSIUM CARBONATE 0.08 g/80 mL
INACTIVE INGREDIENTS: HYPROMELLOSES; CITRIC ACID MONOHYDRATE; WATER; CALCIUM HYDROXIDE

MOONSTAR HAIR MIST

Active ingredient

Potassium carbonate (0.1%)

Purpose

antibacterial

Uses

Sanitizer to help decrease bacteria on scalp. Helps to clean and hydrate hair and scalp. To stimulate hair growth and thicken hair.

Warnings

For external use only

Do not use when scalp is red, inflamed, irritated, or painful

When using this product

- do not use on damaged or broken scalp
- avoid contact with eyes. If contact occurs, rinse eyes thoroughly with water
- do not apply directly to wound or open cut

Stop use and ask a doctor if

- Rash or irritation on scalp develops and lasts

Keep out of reach of children

If swallowed, get medical help or contact a Poison Control Center (1-800-222-1222) right away.

Directions

Mist hair and scalp daily to cleanse, hydrate, and nourish.

Inactive ingredients

Distilled Water, ε-Polylysine, Hydroxypropylmethyl Cellulose, Citric Acid, Tea Catechin, Calcium hydroxide